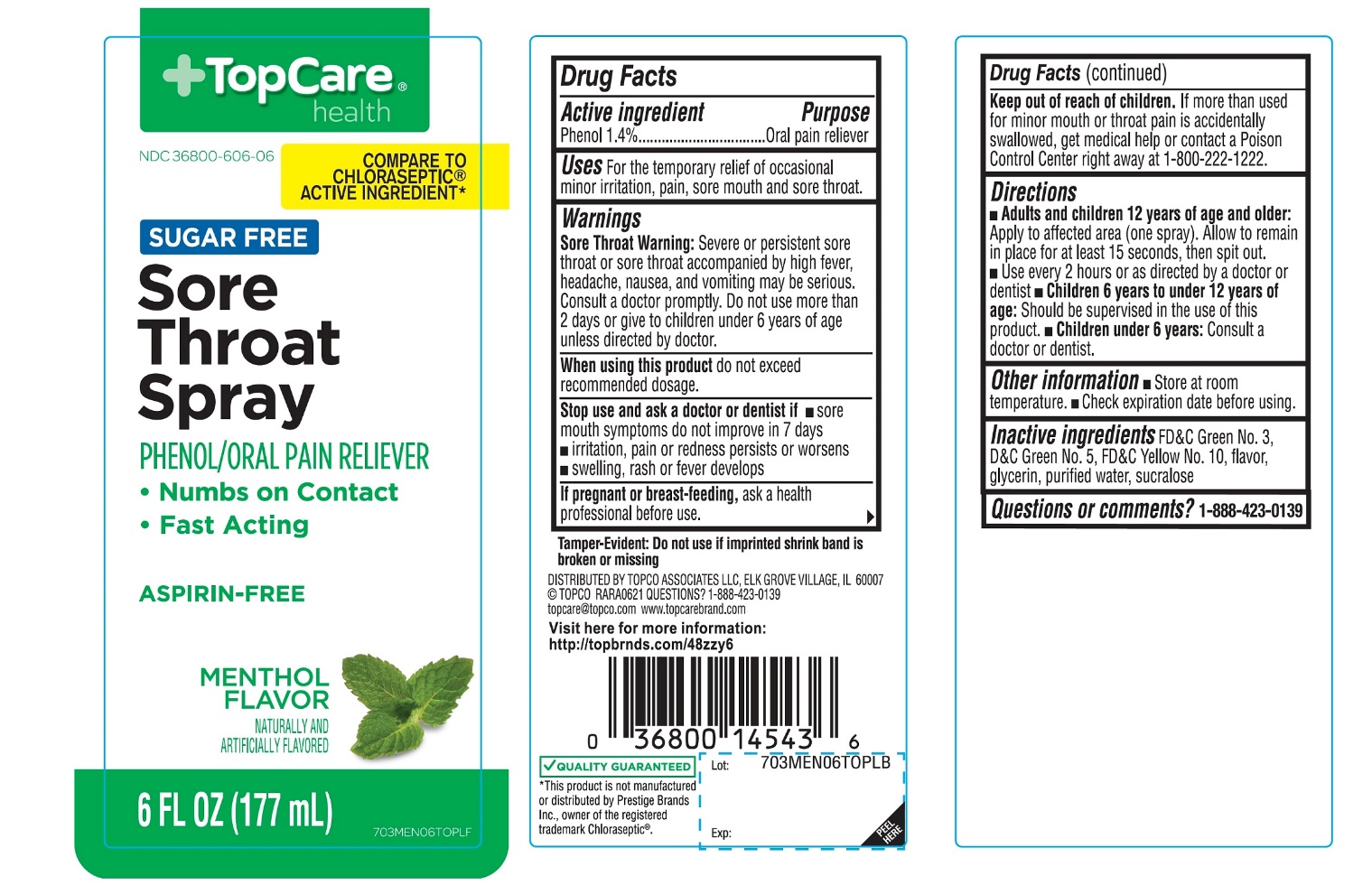 DRUG LABEL: Topcare Sore Throat

NDC: 36800-606 | Form: SPRAY
Manufacturer: TOPCO ASSOCIATES LLC
Category: otc | Type: HUMAN OTC DRUG LABEL
Date: 20251110

ACTIVE INGREDIENTS: PHENOL 1.4 g/100 mL
INACTIVE INGREDIENTS: FD&C GREEN NO. 3; D&C GREEN NO. 5; D&C YELLOW NO. 10; GLYCERIN; WATER; SUCRALOSE

TopCare Sore Throat Spray Sugar Free

Active ingredient

Phenol 1.4%

Purpose

Oral anesthetic/analgesic

Uses

For the temporarily relieves of occasional minor irritation, pain, sore mouth and sore throat.

Warnings

Sore throat warning:Severe or persistent sore throat or sore throat accompanied by high fever, headache, nausea, and vomiting may be serious. Consult a doctor promptly. Do not use more than 2 days or administer to children under 6 year of age unless directed by doctor.

When using this product,

do not exceed recommended dosage.

Stop use and ask a doctor or dentist if

- sore mouth symptoms do not improve in 7 days
- irritation, pain or redness persists or worsens
- swelling, rash or fever develops

If pregnant or breast-feeding,

ask a doctor before use.

Keep out of reach of children.

In case of overdose or accidental,get medical help or contact a Poison Control Center right away (1-800-222-1222).

Directions

- Adults and children 12 year of age and older:

Apply to affected area (one spray). Allow to remain in place for at least 15 seconds, then spit out.

Use every 2 hours or as directed by a doctor or dentist

- Children under 12 years of age:Should be supervised in use of this product.
- Children under 6 years of age: Ask a doctor or dentist

Other information

- store at room temperature
- Check expiration date before using.

Inactive ingredients

FD&C Green No.3, D&C Green No. 5, D&C Yellow No.10, flavor, glycerin, purified water, sucralose.

Questions or comments?

1-888-423-0139

Principal Display Panel

TopCare®health™

NDC# 36800-606-06

COMPARE TO THE CHLORASEPTIC® ACTIVE INGREDIENT*

SUGAR FREE

Sore Throat Spray

PHENOL / ORAL ANESTHETIC

- Works on Contact
- Relieves Sore Throat Pain
- Fast Acting

ASPIRIN FREE

ALCOHOL FREE

MENTHOL FLAVOR

OUR PHARMACIST RECOMMEND

6 FL OZ (177 mL)

QUALITY GUARANTEED

*This product is not manufactured or distributed by Prestige Brands Co., distributor of Chloraseptic®.

TAMPER EVIDENT: DO NOT USE IF IMPRINTED SHRINK BAND IS BROKEN OR TORN.

DISTRIBUTED BY TOPCO ASSOCIATESLLC,

ELK GROVE VILLAGE, IL 6007

TOPCO RARA1217

QUESTIONS? 1-888-423-0139

topcare@topco.comwww.tocarebrand.com